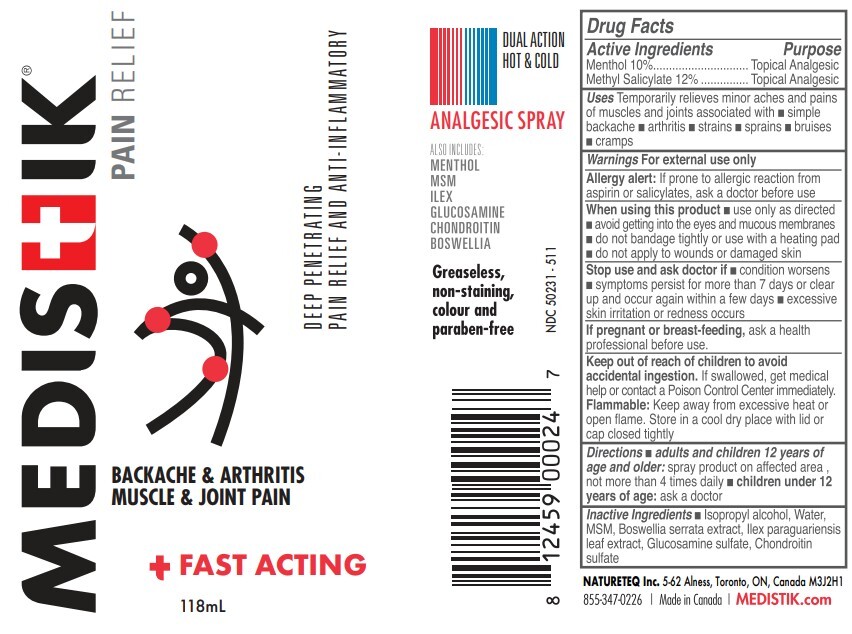 DRUG LABEL: MEDISTIK DUAL HOT AND COLD
NDC: 50231-511 | Form: SPRAY
Manufacturer: Natureteq Inc.
Category: otc | Type: HUMAN OTC DRUG LABEL
Date: 20250915

ACTIVE INGREDIENTS: MENTHOL 10 g/100 mL; METHYL SALICYLATE 12 g/100 mL
INACTIVE INGREDIENTS: WATER; ISOPROPYL ALCOHOL; BOSWELLIA SERRATA WHOLE; ILEX PARAGUARIENSIS LEAF; GLUCOSAMINE SULFATE; CHONDROITIN SULFATE (CHICKEN)

Natureteq (as PLD) - MEDISTIK DUAL ACTION (50231-511)

ACTIVE INGREDIENTS

Methyl Salicylate 12%

Menthol 10%

PURPOSE

Topical Analgesic

USES

Provides temporary soothing relief of sore muscles associated with strains and sprains, backaches, lumbago, pain of tendons
and/or ligaments as well as arthritic or rheumatic pain

WARNINGS

For external use only. Avoid contact with the eyes and mucous membranes. Do not apply to wounds or damaged skin. Do not tightly bandage. Do not inhale. Do not apply with external heat, such as an electric heating pad, as this may result in excessive skin irritation or skin burn. Keep out of the reach of children. If overdose or accidental ingestion occurs, call a Poison Control Center immediately. Consult your health care practitioner prior to use if you are pregnant or breastfeeding or if you are taking anti-coagulant medications or if you are taking medication or natural health products that cause dilation of blood vessels. Rashes and/or burning discomfort and hypersensitivity such as allergy have been known to occur; in which case; discontinue use.

DIRECTIONS

For use on adults and children over 12 years of age. For children (12 years old): Application should be supervised by an adult. Apply thinly and evenly to affected area up to 3 to 4 times per day. Rub and/or massage into skin until solution vanishes. A stinging or burning sensation will be experienced during the first few minutes as the formula begins working. For arthritis or muscle pain of the hands, retain for at least 10 minutes then wash hands. Consult your health care practitioner for use beyond 7 days

INACTIVE INGREDIENTS

Isopropyl alcohol, Water, MSM, Boswellia serrata extract, Ilex paraguariensis leaf extract, Glucosamine sulphate, Chondroitin sulphate.

KEEP OUT OF REACH OF CHILDREN